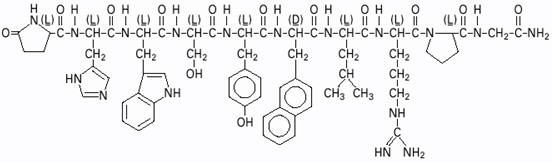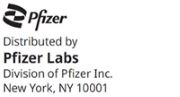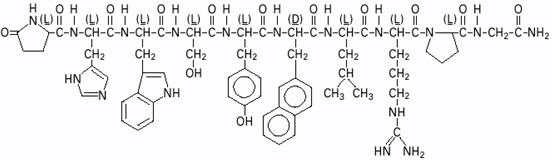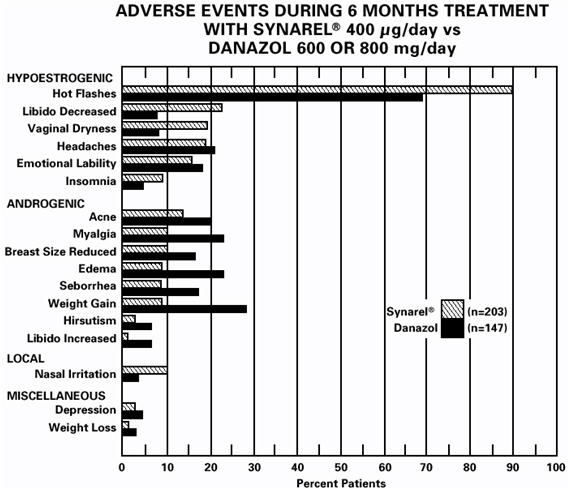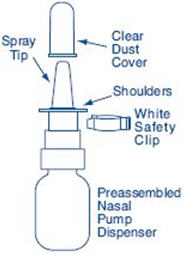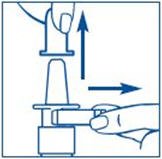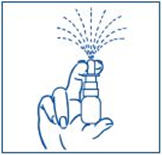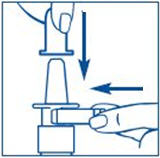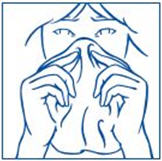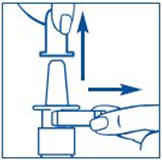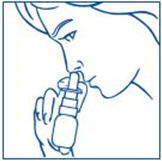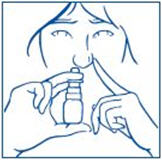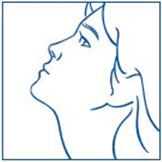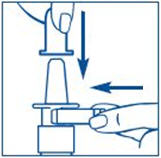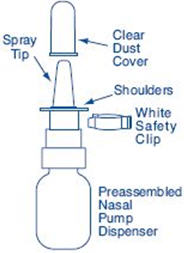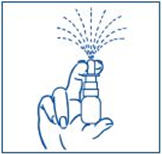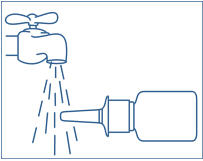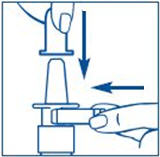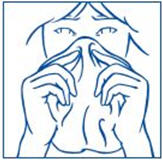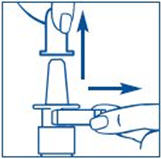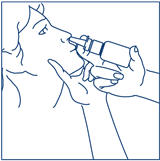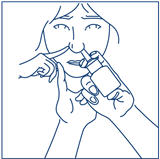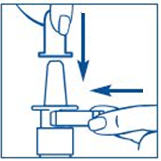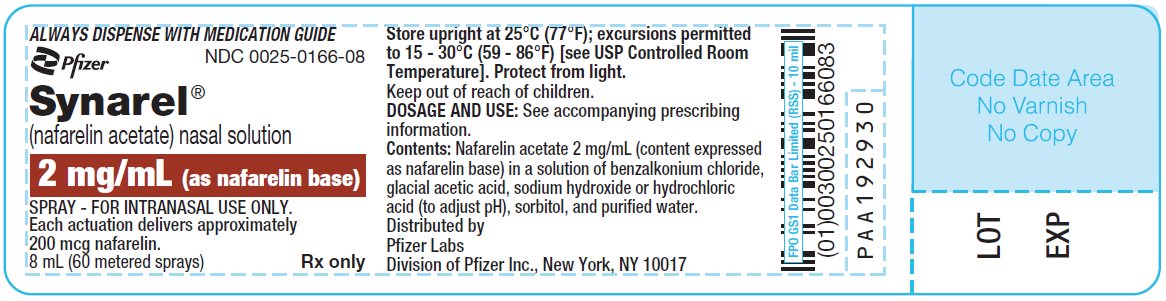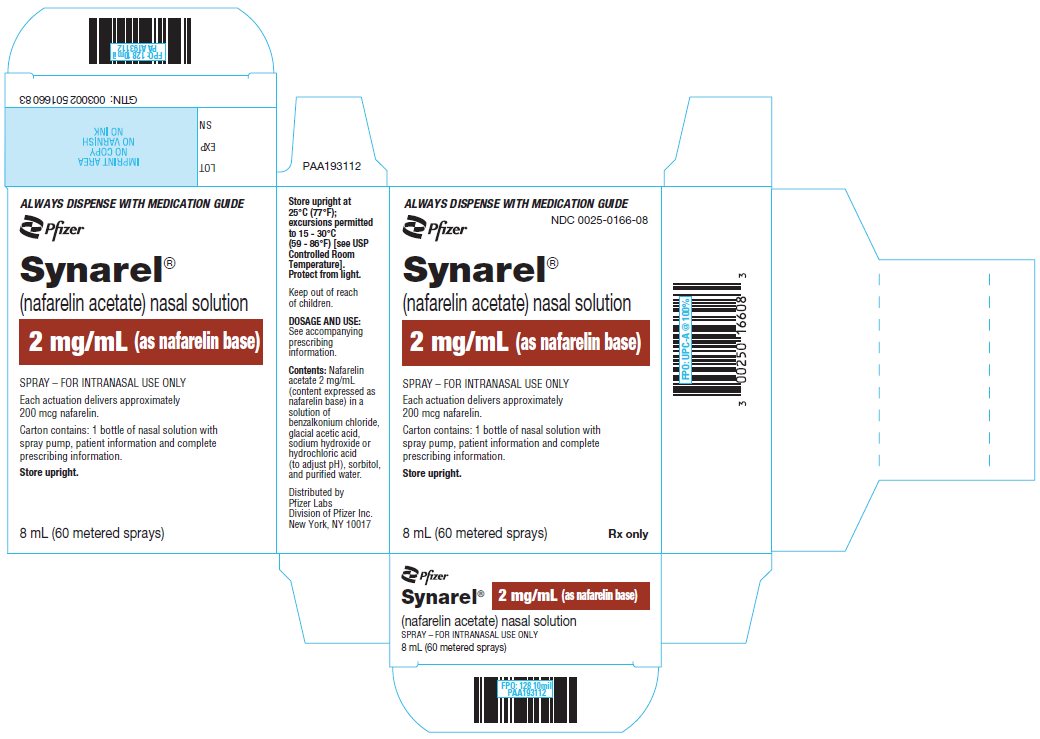 DRUG LABEL: Synarel
NDC: 0025-0166 | Form: SPRAY, METERED
Manufacturer: Pfizer Laboratories Div Pfizer Inc
Category: prescription | Type: HUMAN PRESCRIPTION DRUG LABEL
Date: 20251218

ACTIVE INGREDIENTS: NAFARELIN ACETATE 2 mg/1 mL
INACTIVE INGREDIENTS: BENZALKONIUM CHLORIDE; ACETIC ACID; SODIUM HYDROXIDE; HYDROCHLORIC ACID; SORBITOL; WATER

Synarel®
(nafarelin acetate)
nasal solution

CENTRAL PRECOCIOUS PUBERTY (FOR ENDOMETRIOSIS, SEE REVERSE SIDE)

PHYSICIAN LABELING

DESCRIPTION

SYNAREL (nafarelin acetate) Nasal Solution is intended for administration as a spray to the nasal mucosa. Nafarelin acetate, the active component of SYNAREL Nasal Solution, is a decapeptide with the chemical name: 5-oxo-L-prolyl-L-histidyl-L-tryptophyl-L-seryl-L-tyrosyl-3-(2-naphthyl)-D-alanyl-L-leucyl-L-arginyl-L-prolyl-glycinamide acetate. Nafarelin acetate is a synthetic analog of the naturally occurring gonadotropin-releasing hormone (GnRH).

Nafarelin acetate has the following chemical structure:

∙ x CH3COOH ∙ y H2O (1 ⩽ x ⩽ 2; 2 ⩽ y ⩽ 8)

SYNAREL Nasal Solution contains nafarelin acetate (2 mg/mL, content expressed as nafarelin base) in a solution of benzalkonium chloride, glacial acetic acid, sodium hydroxide or hydrochloric acid (to adjust pH), sorbitol, and purified water.

After priming the pump unit for SYNAREL, each actuation of the unit delivers approximately 100 µL of the spray containing approximately 200 µg nafarelin base. The contents of one spray bottle are intended to deliver at least 60 sprays.

CLINICAL PHARMACOLOGY

Nafarelin acetate is a potent agonistic analog of gonadotropin-releasing hormone (GnRH). At the onset of administration, nafarelin stimulates the release of the pituitary gonadotropins, LH and FSH, resulting in a temporary increase of gonadal steroidogenesis. Repeated dosing abolishes the stimulatory effect on the pituitary gland. Twice daily administration leads to decreased secretion of gonadal steroids by about 4 weeks; consequently, tissues and functions that depend on gonadal steroids for their maintenance become quiescent.

In children, nafarelin acetate was rapidly absorbed into the systemic circulation after intranasal administration. Maximum serum concentrations (measured by RIA) were achieved between 10 and 45 minutes. Following a single dose of 400 µg base, the observed peak concentration was 2.2 ng/mL, whereas following a single dose of 600 µg base, the observed peak concentration was 6.6 ng/mL. The average serum half-life of nafarelin following intranasal administration of a 400 µg dose was approximately 2.5 hours. It is not known and cannot be predicted what the pharmacokinetics of nafarelin will be in children given a dose above 600 µg.

In adult women, nafarelin acetate was rapidly absorbed into the systemic circulation after intranasal administration. Maximum serum concentrations (measured by RIA) were achieved between 10 and 40 minutes. Following a single dose of 200 µg base, the observed average peak concentration was 0.6 ng/mL (range 0.2 to 1.4 ng/mL), whereas following a single dose of 400 µg base, the observed average peak concentration was 1.8 ng/mL (range 0.5 to 5.3 ng/mL). Bioavailability from a 400 µg dose averaged 2.8% (range 1.2 to 5.6%). The average serum half-life of nafarelin following intranasal administration was approximately 3 hours. About 80% of nafarelin acetate was bound to plasma proteins at 4°C. Twice daily intranasal administration of 200 or 400 µg of SYNAREL in 18 healthy women for 22 days did not lead to significant accumulation of the drug. Based on the mean Cmin levels on Days 15 and 22, there appeared to be dose proportionality across the two dose levels.

After subcutaneous administration of ^14C-nafarelin acetate to men, 44–55% of the dose was recovered in urine and 18.5–44.2% was recovered in feces. Approximately 3% of the administered dose appeared as unchanged nafarelin in urine. The ^14C serum half-life of the metabolites was about 85.5 hours. Six metabolites of nafarelin have been identified of which the major metabolite is Tyr-D(2)-Nal-Leu-Arg-Pro-Gly-NH2(5–10). The activity of the metabolites, the metabolism of nafarelin by nasal mucosa, and the pharmacokinetics of the drug in hepatically- and renally-impaired patients have not been determined.

There appeared to be no significant effect of rhinitis, i.e., nasal congestion, on the systemic bioavailability of SYNAREL; however, if the use of a nasal decongestant for rhinitis is necessary during treatment with SYNAREL, the decongestant should not be used until at least 2 hours following dosing with SYNAREL.

When used regularly in girls and boys with central precocious puberty (CPP) at the recommended dose, SYNAREL suppresses LH and sex steroid hormone levels to prepubertal levels, affects a corresponding arrest of secondary sexual development, and slows linear growth and skeletal maturation. In some cases, initial estrogen withdrawal bleeding may occur, generally within 6 weeks after initiation of therapy. Thereafter, menstruation should cease.

In clinical studies the peak response of LH to GnRH stimulation was reduced from a pubertal response to a prepubertal response (<15 mlU/mL) within one month of treatment.

Linear growth velocity, which is commonly pubertal in children with CPP, is reduced in most children within the first year of treatment to values of 5 to 6 cm/year or less. Children with CPP are frequently taller than their chronological age peers; height for chronological age approaches normal in most children during the second or third year of treatment with SYNAREL. Skeletal maturation rate (bone age velocity—change in bone age divided by change in chronological age) is usually abnormal (greater than 1) in children with CPP; in most children, bone age velocity approaches normal (1) during the first year of treatment. This results in a narrowing of the gap between bone age and chronological age, usually by the second or third year of treatment. The mean predicted adult height increases.

In clinical trials, breast development was arrested or regressed in 82% of girls, and genital development was arrested or regressed in 100% of boys. Because pubic hair growth is largely controlled by adrenal androgens, which are unaffected by nafarelin, pubic hair development was arrested or regressed only in 54% of girls and boys.

Reversal of the suppressive effects of SYNAREL has been demonstrated to occur in all children with CPP for whom one-year post-treatment follow-up is available (n=69). This demonstration consisted of the appearance or return of menses, the return of pubertal gonadotropin and gonadal sex steroid levels, and/or the advancement of secondary sexual development. Semen analysis was normal in the two ejaculated specimens obtained thus far from boys who have been taken off therapy to resume puberty. Fertility has not been documented by pregnancies and the effect of long-term use of the drug on fertility is not known.

INDICATIONS AND USAGE FOR CENTRAL PRECOCIOUS PUBERTY

(For Endometriosis, See Reverse Side)

SYNAREL is indicated for treatment of central precocious puberty (CPP) (gonadotropin-dependent precocious puberty) in children of both sexes.

The diagnosis of central precocious puberty (CPP) is suspected when premature development of secondary sexual characteristics occurs at or before the age of 8 years in girls and 9 years in boys, and is accompanied by significant advancement of bone age and/or a poor adult height prediction. The diagnosis should be confirmed by pubertal gonadal sex steroid levels and a pubertal LH response to stimulation by native GnRH. Pelvic ultrasound assessment in girls usually reveals enlarged uterus and ovaries, the latter often with multiple cystic formations. Magnetic resonance imaging or CT-scanning of the brain is recommended to detect hypothalamic or pituitary tumors, or anatomical changes associated with increased intracranial pressure. Other causes of sexual precocity, such as congenital adrenal hyperplasia, testotoxicosis, testicular tumors and/or other autonomous feminizing or masculinizing disorders must be excluded by proper clinical hormonal and diagnostic imaging examinations.

CONTRAINDICATIONS

1. Hypersensitivity to GnRH, GnRH agonist analogs or any of the excipients in SYNAREL;

2. Undiagnosed abnormal vaginal bleeding;

3. Use in pregnancy or in women who may become pregnant while receiving the drug. SYNAREL may cause fetal harm when administered to a pregnant woman. Major fetal abnormalities were observed in rats, but not in mice or rabbits after administration of SYNAREL during the period of organogenesis. There was a dose-related increase in fetal mortality and a decrease in fetal weight in rats [see Pregnancy]. The effects on rat fetal mortality are expected consequences of the alterations in hormonal levels brought about by the drug. If this drug is used during pregnancy or if the patient becomes pregnant while taking this drug, she should be apprised of the potential hazard to the fetus;

4. Use in women who are breast-feeding [see Nursing Mothers].

WARNINGS

The diagnosis of central precocious puberty (CPP) must be established before treatment is initiated. Regular monitoring of CPP patients is needed to assess both patient response as well as compliance. This is particularly important during the first 6 to 8 weeks of treatment to assure that suppression of pituitary-gonadal function is rapid. Testing may include LH response to GnRH stimulation and circulating gonadal sex steroid levels. Assessment of growth velocity and bone age velocity should begin within 3 to 6 months of treatment initiation.

Some patients may not show suppression of the pituitary-gonadal axis by clinical and/or biochemical parameters. This may be due to lack of compliance with the recommended treatment regimen and may be rectified by recommending that the dosing be done by caregivers. If compliance problems are excluded, the possibility of gonadotropin independent sexual precocity should be reconsidered and appropriate examinations should be conducted. If compliance problems are excluded and if gonadotropin independent sexual precocity is not present, the dose of SYNAREL may be increased to 1800 µg/day administered as 600 µg tid.

Psychiatric events have been reported in patients taking GnRH agonists. Postmarketing reports with this class of drugs includes symptoms of emotional lability, such as crying, irritability, impatience, anger, and aggression. Monitor for development or worsening of psychiatric symptoms during treatment with SYNAREL.

Post-marketing reports of convulsions have been observed in patients receiving GnRH agonists. These have included patients with a history of seizures, epilepsy, cerebrovascular disorders, central nervous system anomalies or tumors, and patients on concomitant medications that have been associated with convulsions such as bupropion and SSRIs. Convulsions have also been reported in patients in the absence of any of the conditions mentioned above.

Severe cutaneous adverse reactions (SCARs) have been reported in patients receiving other GnRH agonists. These reactions include Stevens-Johnson syndrome/toxic epidermal necrolysis (SJS/TEN), drug reaction with eosinophilia and systemic symptoms (DRESS), and acute generalized exanthematous pustulosis (AGEP), including cases with visceral involvement and/or requiring skin grafts. If a SCAR is suspected, discontinue SYNAREL. Consult with a healthcare provider with expertise in the diagnosis and management of SCARs. If a diagnosis of SCAR is confirmed, permanently discontinue SYNAREL.

Pseudotumor cerebri (idiopathic intracranial hypertension) has been reported in pediatric patients receiving GnRH agonists. Monitor patients for signs and symptoms of pseudotumor cerebri, including headache, papilledema, blurred vision, diplopia, loss of vision, pain behind the eye or pain with eye movement, tinnitus, dizziness, and nausea.

PRECAUTIONS

General

As with other drugs that stimulate the release of gonadotropins or that induce ovulation, in adult women with endometriosis ovarian cysts have been reported to occur in the first two months of therapy with SYNAREL. Many, but not all, of these events occurred in women with polycystic ovarian disease. These cystic enlargements may resolve spontaneously, generally by about four to six weeks of therapy, but in some cases may require discontinuation of drug and/or surgical intervention. The relevance, if any, of such events in children is unknown.

Information for Patients, Patients' Parents or Guardians

An information pamphlet for patients is included with the product. Patients and their caregivers should be aware of the following information:

1. Reversibility of the suppressive effects of nafarelin has been demonstrated by the appearance or return of menses, by the return of pubertal gonadotropin and gonadal sex steroid levels, and/or by advancement of secondary sexual development. Semen analysis was normal in the two ejaculated specimens obtained thus far from boys who have been taken off therapy to resume puberty. Fertility has not been documented by pregnancies and the effect of long-term use of the drug on fertility is not known.

2. Patients and their caregivers should be adequately counseled to assure full compliance; irregular or incomplete daily doses may result in stimulation of the pituitary-gonadal axis.

3. Inform parents and caregivers that reports of convulsions have been observed in patients receiving GnRH agonists. Patients with a history of seizures, epilepsy, cerebrovascular disorders, central nervous system anomalies or tumors, and patients on concomitant medications that have been associated with convulsions may be at increased risk [see Warnings].

4. Inform patients and caregivers that reports of pseudotumor cerebri (idiopathic intracranial hypertension) have been observed in pediatric patients receiving GnRH agonists. Advise patients and caregivers to monitor for headache, and vision issues such as blurred vision, double vision, loss of vision, pain behind the eye or pain with eye movement, ringing in the ears, dizziness, and nausea. Advise patients and caregivers to contact their healthcare provider if the patient develops any of these symptoms [see Warnings].

5. During the first month of treatment with SYNAREL, some signs of puberty, e.g., vaginal bleeding or breast enlargement, may occur. This is the expected initial effect of the drug. Such changes should resolve soon after the first month. If such resolution does not occur within the first two months of treatment, this may be due to lack of compliance or the presence of gonadotropin independent sexual precocity. If both possibilities are definitively excluded, the dose of SYNAREL may be increased to 1800 µg/day administered as 600 µg tid.

6. Patients with intercurrent rhinitis should consult their physician for the use of a topical nasal decongestant. If the use of a topical nasal decongestant is required during treatment with SYNAREL, the decongestant should not be used until at least 2 hours following dosing with SYNAREL.

Sneezing during or immediately after dosing with SYNAREL should be avoided, if possible, since this may impair drug absorption.

Drug Interactions

No pharmacokinetic-based drug-drug interaction studies have been conducted with SYNAREL. However, because nafarelin acetate is a peptide that is primarily degraded by peptidase and not by cytochrome P-450 enzymes, and the drug is only about 80% bound to plasma proteins at 4°C, drug interactions would not be expected to occur.

Carcinogenesis, Mutagenesis, Impairment of Fertility

Carcinogenicity studies of nafarelin were conducted in rats (24 months) at doses up to 100 µg/kg/day and mice (18 months) at doses up to 500 µg/kg/day using intramuscular doses (up to 110 times and 560 times the maximum recommended human intranasal dose, respectively). These multiples of the human dose are based on the relative bioavailability of the drug by the two routes of administration. As seen with other GnRH agonists, nafarelin acetate given to laboratory rodents at high doses for prolonged periods induced proliferative responses (hyperplasia and/or neoplasia) of endocrine organs. At 24 months, there was an increase in the incidence of pituitary tumors (adenoma/carcinoma) in high-dose female rats and a dose-related increase in male rats. There was an increase in pancreatic islet cell adenomas in both sexes, and in benign testicular and ovarian tumors in the treated groups. There was a dose-related increase in benign adrenal medullary tumors in treated female rats. In mice, there was a dose-related increase in Harderian gland tumors in males and an increase in pituitary adenomas in high-dose females. No metastases of these tumors were observed. It is known that tumorigenicity in rodents is particularly sensitive to hormonal stimulation.

Mutagenicity studies were performed with nafarelin acetate using bacterial, yeast, and mammalian systems. These studies provided no evidence of mutagenic potential.

Reproduction studies in male and female rats have shown full reversibility of fertility suppression when drug treatment was discontinued after continuous administration for up to 6 months. The effect of treatment of prepubertal rats on the subsequent reproductive performance of mature animals has not been investigated.

Pregnancy

Teratogenic Effects

See Contraindications. Intramuscular SYNAREL was administered to rats during the period of organogenesis at 0.4, 1.6, and 6.4 µg/kg/day (about 0.5, 2, and 7 times the maximum recommended human intranasal dose based on the relative bioavailability by the two routes of administration). An increase in major fetal abnormalities was observed in 4/80 fetuses at the highest dose. A similar, repeat study at the same doses in rats and studies in mice and rabbits at doses up to 600 µg/kg/day and 0.18 µg/kg/day, respectively, failed to demonstrate an increase in fetal abnormalities after administration during the period of organogenesis. In rats and rabbits, there was a dose-related increase in fetal mortality and a decrease in fetal weight with the highest dose.

Nursing Mothers

It is not known whether SYNAREL is excreted in human milk. Because many drugs are excreted in human milk, and because the effects of SYNAREL on lactation and/or the breastfed child have not been determined, SYNAREL should not be used by nursing mothers.

ADVERSE REACTIONS

In clinical trials of 155 pediatric patients, 2.6% reported symptoms suggestive of drug sensitivity, such as shortness of breath, chest pain, urticaria, rash, and pruritus.

In these 155 patients treated for an average of 41 months and as long as 80 months (6.7 years), adverse events most frequently reported (>3% of patients) consisted largely of episodes occurring during the first 6 weeks of treatment as a result of the transient stimulatory action of nafarelin upon the pituitary-gonadal axis:

acne (10%)
transient breast enlargement (8%)
vaginal bleeding (8%)
emotional lability (6%) [see Warnings]
transient increase in pubic hair (5%)
body odor (4%)
seborrhea (3%)

Hot flashes, common in adult women treated for endometriosis, occurred in only 3% of treated children and were transient. Other adverse events thought to be drug-related, and occurring in >3% of patients were rhinitis (5%) and white or brownish vaginal discharge (3%). Approximately 3% of patients withdrew from clinical trials due to adverse events.

In one male patient with concomitant congenital adrenal hyperplasia, and who had discontinued treatment 8 months previously to resume puberty, adrenal rest tumors were found in the left testis. Relationship to SYNAREL is unlikely.

Regular examinations of the pituitary gland by magnetic resonance imaging (MRI) or computer assisted tomography (CT) of children during long-term nafarelin therapy as well as during the post-treatment period has occasionally revealed changes in the shape and size of the pituitary gland. These changes include asymmetry and enlargement of the pituitary gland, and a pituitary microadenoma has been suspected in a few children. The relationship of these findings to SYNAREL is not known.

Post-Marketing

Pituitary apoplexy: During post-marketing surveillance, rare cases of pituitary apoplexy (a clinical syndrome secondary to infarction of the pituitary gland) have been reported after the administration of gonadotropin-releasing hormone agonists. In a majority of these cases, a pituitary adenoma was diagnosed, with a majority of pituitary apoplexy cases occurring within 2 weeks of the first dose, and some within the first hour. In these cases, pituitary apoplexy has presented as sudden headache, vomiting, visual changes, ophthalmoplegia, altered mental status, and sometimes cardiovascular collapse. Immediate medical attention has been required.

Psychiatric adverse events: Emotional lability, such as crying, irritability, impatience, anger, and aggression has been observed with GnRH agonists [see Warnings]; Depression, including rare reports of suicidal ideation and attempt, has been reported for GnRH agonists in children treated for central precocious puberty. Many, but not all, of these patients had a history of psychiatric illness or other comorbidities with an increased risk of depression.

Central/peripheral nervous adverse events: Convulsion, pseudotumor cerebri (idiopathic intracranial hypertension).

OVERDOSAGE

In experimental animals, a single subcutaneous administration of up to 60 times the recommended human dose (on a µg/kg basis, not adjusted for bioavailability) had no adverse effects. At present, there is no clinical evidence of adverse effects following overdosage of GnRH analogs.

Based on studies in monkeys, SYNAREL is not absorbed after oral administration.

DOSAGE AND ADMINISTRATION

For the treatment of central precocious puberty (CPP), the recommended daily dose of SYNAREL is 1600 µg. The dose can be increased to 1800 µg daily if adequate suppression cannot be achieved at 1600 µg/day.

The 1600 µg dose is achieved by two sprays (400 µg) into each nostril in the morning (4 sprays) and two sprays into each nostril in the evening (4 sprays), a total of 8 sprays per day. The 1800 µg dose is achieved by 3 sprays (600 µg) into alternating nostrils three times a day, a total of 9 sprays per day. The patient's head should be tilted back slightly, and 30 seconds should elapse between sprays.

If the prescribed therapy has been well tolerated by the patient, treatment of CPP with SYNAREL should continue until resumption of puberty is desired.

There appeared to be no significant effect of rhinitis, i.e., nasal congestion, on the systemic bioavailability of SYNAREL; however, if the use of a nasal decongestant for rhinitis is necessary during treatment with SYNAREL, the decongestant should not be used until at least 2 hours following dosing with SYNAREL.

Sneezing during or immediately after dosing with SYNAREL should be avoided, if possible, since this may impair drug absorption.

At 1600 µg/day, a bottle of SYNAREL provides about a 7-day supply (about 56 sprays). If the daily dose is increased, increase the supply to the patient to ensure uninterrupted treatment for the duration of therapy.

HOW SUPPLIED

Each 0.5 ounce bottle (NDC 0025-0166-08) contains 8 mL SYNAREL (nafarelin acetate) Nasal Solution 2 mg/mL (as nafarelin base), and is supplied with a metered spray pump that delivers 200 µg of nafarelin per spray. A dust cover and a leaflet of patient instructions are also included.

STORAGE AND HANDLING

Store upright at 25°C (77°F); excursions permitted to 15–30°C (59–86°F) [see USP Controlled Room Temperature]. Protect from light.

LAB-1048-5.0
Revised: November 2025

Synarel®
(nafarelin acetate)
nasal solution

ENDOMETRIOSIS (FOR CENTRAL PRECOCIOUS PUBERTY, SEE REVERSE SIDE)

PHYSICIAN LABELING

DESCRIPTION

SYNAREL (nafarelin acetate) Nasal Solution is intended for administration as a spray to the nasal mucosa. Nafarelin acetate, the active component of SYNAREL Nasal Solution, is a decapeptide with the chemical name: 5-oxo-L-prolyl-L-histidyl-L-tryptophyl-L-seryl-L-tyrosyl-3-(2-naphthyl)-D-alanyl-L-leucyl-L-arginyl-L-prolyl-glycinamide acetate. Nafarelin acetate is a synthetic analog of the naturally occurring gonadotropin-releasing hormone (GnRH).

Nafarelin acetate has the following chemical structure:

∙ x CH3COOH ∙ y H2O (1 ⩽ x ⩽ 2; 2 ⩽ y ⩽ 8)

SYNAREL Nasal Solution contains nafarelin acetate (2 mg/mL, content expressed as nafarelin base) in a solution of benzalkonium chloride, glacial acetic acid, sodium hydroxide or hydrochloric acid (to adjust pH), sorbitol, and purified water.

After priming the pump unit for SYNAREL, each actuation of the unit delivers approximately 100 µL of the spray containing approximately 200 µg nafarelin base. The contents of one spray bottle are intended to deliver at least 60 sprays.

CLINICAL PHARMACOLOGY

Nafarelin acetate is a potent agonistic analog of gonadotropin-releasing hormone (GnRH). At the onset of administration, nafarelin stimulates the release of the pituitary gonadotropins, LH and FSH, resulting in a temporary increase of ovarian steroidogenesis. Repeated dosing abolishes the stimulatory effect on the pituitary gland. Twice daily administration leads to decreased secretion of gonadal steroids by about 4 weeks; consequently, tissues and functions that depend on gonadal steroids for their maintenance become quiescent.

Nafarelin acetate is rapidly absorbed into the systemic circulation after intranasal administration. Maximum serum concentrations (measured by RIA) were achieved between 10 and 40 minutes. Following a single dose of 200 µg base, the observed average peak concentration was 0.6 ng/mL (range 0.2 to 1.4 ng/mL), whereas following a single dose of 400 µg base, the observed average peak concentration was 1.8 ng/mL (range 0.5 to 5.3 ng/mL). Bioavailability from a 400 µg dose averaged 2.8% (range 1.2 to 5.6%). The average serum half-life of nafarelin following intranasal administration is approximately 3 hours. About 80% of nafarelin acetate is bound to plasma proteins at 4°C. Twice daily intranasal administration of 200 or 400 µg of SYNAREL in 18 healthy women for 22 days did not lead to significant accumulation of the drug. Based on the mean Cmin levels on Days 15 and 22, there appeared to be dose proportionality across the two dose levels.

After subcutaneous administration of ^14C-nafarelin acetate to men, 44–55% of the dose was recovered in urine and 18.5–44.2% was recovered in feces. Approximately 3% of the administered dose appeared as unchanged nafarelin in urine. The ^14C serum half-life of the metabolites was about 85.5 hours. Six metabolites of nafarelin have been identified of which the major metabolite is Tyr-D(2)-Nal-Leu-Arg-Pro-Gly-NH2(5–10). The activity of the metabolites, the metabolism of nafarelin by nasal mucosa, and the pharmacokinetics of the drug in hepatically- and renally-impaired patients have not been determined.

There appeared to be no significant effect of rhinitis, i.e., nasal congestion, on the systemic bioavailability of SYNAREL; however, if the use of a nasal decongestant for rhinitis is necessary during treatment with SYNAREL, the decongestant should not be used until at least 2 hours following dosing of SYNAREL.

In controlled clinical studies, SYNAREL at doses of 400 and 800 µg/day for 6 months was shown to be comparable to danazol, 800 mg/day, in relieving the clinical symptoms of endometriosis (pelvic pain, dysmenorrhea, and dyspareunia) and in reducing the size of endometrial implants as determined by laparoscopy. The clinical significance of a decrease in endometriotic lesions is not known at this time and, in addition, laparoscopic staging of endometriosis does not necessarily correlate with severity of symptoms.

In a single controlled clinical trial, intranasal SYNAREL (nafarelin acetate) at a dose of 400 µg per day was shown to be clinically comparable to intramuscular leuprolide depot, 3.75 mg monthly, for the treatment of the symptoms (dysmenorrhea, dyspareunia and pelvic pain) associated with endometriosis.

SYNAREL 400 µg daily induced amenorrhea in approximately 65%, 80%, and 90% of the patients after 60, 90, and 120 days, respectively. In the first, second, and third post-treatment months, normal menstrual cycles resumed in 4%, 82%, and 100%, respectively, of those patients who did not become pregnant.

At the end of treatment, 60% of patients who received SYNAREL, 400 µg/day, were symptom free, 32% had mild symptoms, 7% had moderate symptoms, and 1% had severe symptoms. Of the 60% of patients who had complete relief of symptoms at the end of treatment, 17% had moderate symptoms 6 months after treatment was discontinued, 33% had mild symptoms, 50% remained symptom free, and no patient had severe symptoms.

During the first two months use of SYNAREL, some women experience vaginal bleeding of variable duration and intensity. In all likelihood, this bleeding represents estrogen withdrawal bleeding and is expected to stop spontaneously. If vaginal bleeding continues, the possibility of lack of compliance with the dosing regimen should be considered. If the patient is complying carefully with the regimen, an increase in dose to 400 µg twice a day should be considered.

There is no evidence that pregnancy rates are enhanced or adversely affected by the use of SYNAREL.

INDICATIONS AND USAGE FOR ENDOMETRIOSIS

(For Central Precocious Puberty, See Reverse Side)

SYNAREL is indicated for management of endometriosis, including pain relief and reduction of endometriotic lesions. Experience with SYNAREL for the management of endometriosis has been limited to women 18 years of age and older treated for 6 months.

CONTRAINDICATIONS

1. Hypersensitivity to GnRH, GnRH agonist analogs or any of the excipients in SYNAREL;
2. Undiagnosed abnormal vaginal bleeding;
3. Use in pregnancy or in women who may become pregnant while receiving the drug. SYNAREL may cause fetal harm when administered to a pregnant woman. Major fetal abnormalities were observed in rats, but not in mice or rabbits after administration of SYNAREL during the period of organogenesis. There was a dose-related increase in fetal mortality and a decrease in fetal weight in rats [see Pregnancy]. The effects on rat fetal mortality are expected consequences of the alterations in hormonal levels brought about by the drug. If this drug is used during pregnancy or if the patient becomes pregnant while taking this drug, she should be apprised of the potential hazard to the fetus;
4. Use in women who are breast-feeding [see Nursing Mothers].

WARNINGS

Safe use of nafarelin acetate in pregnancy has not been established clinically. Before starting treatment with SYNAREL, pregnancy must be excluded.

When used regularly at the recommended dose, SYNAREL usually inhibits ovulation and stops menstruation. Contraception is not insured, however, by taking SYNAREL, particularly if patients miss successive doses. Therefore, patients should use nonhormonal methods of contraception. Patients should be advised to see their physician if they believe they may be pregnant. If a patient becomes pregnant during treatment, the drug must be discontinued and the patient must be apprised of the potential risk to the fetus.

Clinical Depression

Depression may occur or worsen during treatment with GnRH agonists including SYNAREL 2 mg/mL. Carefully observe women for depression, especially those with a history of depression and consider whether the risks of continuing SYNAREL 2 mg/mL outweigh the benefits. Women with new or worsening depression should be referred to a mental health professional, as appropriate [see Precautions].

Severe cutaneous adverse reactions (SCARs) have been reported in patients receiving other GnRH agonists. These reactions include Stevens-Johnson syndrome/toxic epidermal necrolysis (SJS/TEN), drug reaction with eosinophilia and systemic symptoms (DRESS), and acute generalized exanthematous pustulosis (AGEP), including cases with visceral involvement and/or requiring skin grafts. If a SCAR is suspected, discontinue SYNAREL. Consult with a healthcare provider with expertise in the diagnosis and management of SCARs. If a diagnosis of SCAR is confirmed, permanently discontinue SYNAREL.

PRECAUTIONS

General

As with other drugs that stimulate the release of gonadotropins or that induce ovulation, ovarian cysts have been reported to occur in the first two months of therapy with SYNAREL. Many, but not all, of these events occurred in patients with polycystic ovarian disease. These cystic enlargements may resolve spontaneously, generally by about four to six weeks of therapy, but in some cases may require discontinuation of drug and/or surgical intervention.

Information for Patients

An information pamphlet for patients is included with the product. Patients should be aware of the following information:

1. Since menstruation should stop with effective doses of SYNAREL, the patient should notify her physician if regular menstruation persists. The cause of vaginal spotting, bleeding or menstruation could be noncompliance with the treatment regimen, or it could be that a higher dose of the drug is required to achieve amenorrhea. The patient should be questioned regarding her compliance. If she is careful and compliant, and menstruation persists to the second month, consideration should be given to doubling the dose of SYNAREL. If the patient has missed several doses, she should be counseled on the importance of taking SYNAREL regularly as prescribed.

2. Patients should not use SYNAREL if they are pregnant, breastfeeding, have undiagnosed abnormal vaginal bleeding, or are allergic to any of the ingredients in SYNAREL.

3. Safe use of the drug in pregnancy has not been established clinically. Therefore, a nonhormonal method of contraception should be used during treatment. Patients should be advised that if they miss successive doses of SYNAREL, breakthrough bleeding or ovulation may occur with the potential for conception. If a patient becomes pregnant during treatment, she should discontinue treatment and consult her physician.

4. Those adverse events occurring most frequently in clinical studies with SYNAREL are associated with hypoestrogenism; the most frequently reported are hot flashes, headaches, emotional lability, decreased libido, vaginal dryness, acne, myalgia, and reduction in breast size. Estrogen levels returned to normal after treatment was discontinued. Nasal irritation occurred in about 10% of all patients who used intranasal nafarelin.

5. The induced hypoestrogenic state results in a small loss in bone density over the course of treatment, some of which may not be reversible. During one six-month treatment period, this bone loss should not be important. In patients with major risk factors for decreased bone mineral content such as chronic alcohol and/or tobacco use, strong family history of osteoporosis, or chronic use of drugs that can reduce bone mass such as anticonvulsants or corticosteroids, therapy with SYNAREL may pose an additional risk. In these patients the risks and benefits must be weighed carefully before therapy with SYNAREL is instituted. Repeated courses of treatment with gonadotropin-releasing hormone analogs are not advisable in patients with major risk factors for loss of bone mineral content.

6. Inform patients that depression may occur or worsen during treatment with GnRH agonists, including SYNAREL, especially in patients with a history of depression. Advise patients to immediately report thoughts and behaviors of concern to healthcare providers [see Warnings].

7. Patients with intercurrent rhinitis should consult their physician for the use of a topical nasal decongestant. If the use of a topical nasal decongestant is required during treatment with SYNAREL, the decongestant should not be used until at least 2 hours following dosing with SYNAREL.

Sneezing during or immediately after dosing with SYNAREL should be avoided, if possible, since this may impair drug absorption.

8. Retreatment cannot be recommended since safety data beyond 6 months are not available.

Drug Interactions

No pharmacokinetic-based drug-drug interaction studies have been conducted with SYNAREL. However, because nafarelin acetate is a peptide that is primarily degraded by peptidase and not by cytochrome P-450 enzymes, and the drug is only about 80% bound to plasma proteins at 4°C, drug interactions would not be expected to occur.

Drug/Laboratory Test Interactions

Administration of SYNAREL in therapeutic doses results in suppression of the pituitary-gonadal system. Normal function is usually restored within 4 to 8 weeks after treatment is discontinued. Therefore, diagnostic tests of pituitary gonadotropic and gonadal functions conducted during treatment and up to 4 to 8 weeks after discontinuation of therapy with SYNAREL may be misleading.

Carcinogenesis, Mutagenesis, Impairment of Fertility

Carcinogenicity studies of nafarelin were conducted in rats (24 months) at doses up to 100 µg/kg/day and mice (18 months) at doses up to 500 µg/kg/day using intramuscular doses (up to 110 times and 560 times the maximum recommended human intranasal dose, respectively). These multiples of the human dose are based on the relative bioavailability of the drug by the two routes of administration. As seen with other GnRH agonists, nafarelin acetate given to laboratory rodents at high doses for prolonged periods induced proliferative responses (hyperplasia and/or neoplasia) of endocrine organs. At 24 months, there was an increase in the incidence of pituitary tumors (adenoma/carcinoma) in high-dose female rats and a dose-related increase in male rats. There was an increase in pancreatic islet cell adenomas in both sexes, and in benign testicular and ovarian tumors in the treated groups. There was a dose-related increase in benign adrenal medullary tumors in treated female rats. In mice, there was a dose-related increase in Harderian gland tumors in males and an increase in pituitary adenomas in high-dose females. No metastases of these tumors were observed. It is known that tumorigenicity in rodents is particularly sensitive to hormonal stimulation.

Mutagenicity studies were performed with nafarelin acetate using bacterial, yeast, and mammalian systems. These studies provided no evidence of mutagenic potential.

Reproduction studies in male and female rats have shown full reversibility of fertility suppression when drug treatment was discontinued after continuous administration for up to 6 months. The effect of treatment of prepubertal rats on the subsequent reproductive performance of mature animals has not been investigated.

Pregnancy

Teratogenic Effects

See Contraindications. Intramuscular SYNAREL was administered to rats during the period of organogenesis at 0.4, 1.6, and 6.4 µg/kg/day (about 0.5, 2, and 7 times the maximum recommended human intranasal dose based on the relative bioavailability by the two routes of administration). An increase in major fetal abnormalities was observed in 4/80 fetuses at the highest dose. A similar, repeat study at the same doses in rats and studies in mice and rabbits at doses up to 600 µg/kg/day and 0.18 µg/kg/day, respectively, failed to demonstrate an increase in fetal abnormalities after administration during the period of organogenesis. In rats and rabbits, there was a dose-related increase in fetal mortality and a decrease in fetal weight with the highest dose.

Nursing Mothers

It is not known whether SYNAREL is excreted in human milk. Because many drugs are excreted in human milk, and because the effects of SYNAREL on lactation and/or the breastfed child have not been determined, SYNAREL should not be used by nursing mothers.

Pediatric Use

Safety and effectiveness of SYNAREL for endometriosis in patients younger than 18 years have not been established.

ADVERSE REACTIONS

Clinical Studies

In formal clinical trials of 1509 healthy adult patients, symptoms suggestive of drug sensitivity, such as shortness of breath, chest pain, urticaria, rash and pruritus occurred in 3 patients (approximately 0.2%).

As would be expected with a drug which lowers serum estradiol levels, the most frequently reported adverse reactions were those related to hypoestrogenism.

In controlled studies comparing SYNAREL (400 µg/day) and danazol (600 or 800 mg/day), adverse reactions most frequently reported and thought to be drug-related are shown in the figure below:

In addition, less than 1% of patients experienced paresthesia, palpitations, chloasma, maculopapular rash, eye pain, asthenia, lactation, breast engorgement, and arthralgia.

Changes in Bone Density

After six months of treatment with SYNAREL, vertebral trabecular bone density and total vertebral bone mass, measured by quantitative computed tomography (QCT), decreased by an average of 8.7% and 4.3%, respectively, compared to pretreatment levels. There was partial recovery of bone density in the post-treatment period; the average trabecular bone density and total bone mass were 4.9% and 3.3% less than the pretreatment levels, respectively. Total vertebral bone mass, measured by dual photon absorptiometry (DPA), decreased by a mean of 5.9% at the end of treatment.

After six months treatment with SYNAREL, bone mass as measured by dual x-ray bone densitometry (DEXA), decreased 3.2%. Mean total vertebral mass, re-examined by DEXA six months after completion of treatment, was 1.4% below pretreatment. There was little, if any, decrease in the mineral content in compact bone of the distal radius and second metacarpal. Use of SYNAREL for longer than the recommended six months or in the presence of other known risk factors for decreased bone mineral content may cause additional bone loss.

Changes in Laboratory Values During Treatment

Plasma enzymes

During clinical trials with SYNAREL, regular laboratory monitoring revealed that SGOT and SGPT levels were more than twice the upper limit of normal in only one patient each. There was no other clinical or laboratory evidence of abnormal liver function and levels returned to normal in both patients after treatment was stopped.

Lipids

At enrollment, 9% of the patients in the group taking SYNAREL 400 µg/day and 2% of the patients in the danazol group had total cholesterol values above 250 mg/dL. These patients also had cholesterol values above 250 mg/dL at the end of treatment.

Of those patients whose pretreatment cholesterol values were below 250 mg/dL, 6% in the group treated with SYNAREL and 18% in the danazol group, had post-treatment values above 250 mg/dL.

The mean (± SEM) pretreatment values for total cholesterol from all patients were 191.8 (4.3) mg/dL in the group treated with SYNAREL and 193.1 (4.6) mg/dL in the danazol group. At the end of treatment, the mean values for total cholesterol from all patients were 204.5 (4.8) mg/dL in the group treated with SYNAREL and 207.7 (5.1) mg/dL in the danazol group. These increases from the pretreatment values were statistically significant (p<0.05) in both groups.

Triglycerides were increased above the upper limit of 150 mg/dL in 12% of the patients who received SYNAREL and in 7% of the patients who received danazol.

At the end of treatment, no patients receiving SYNAREL had abnormally low HDL cholesterol fractions (less than 30 mg/dL) compared with 43% of patients receiving danazol. None of the patients receiving SYNAREL had abnormally high LDL cholesterol fractions (greater than 190 mg/dL) compared with 15% of those receiving danazol. There was no increase in the LDL/HDL ratio in patients receiving SYNAREL, but there was approximately a 2-fold increase in the LDL/HDL ratio in patients receiving danazol.

Other changes

In comparative studies, the following changes were seen in approximately 10% to 15% of patients. Treatment with SYNAREL was associated with elevations of plasma phosphorus and eosinophil counts, and decreases in serum calcium and WBC counts. Danazol therapy was associated with an increase of hematocrit and WBC.

Post-Marketing

Pituitary apoplexy: During post-marketing surveillance, rare cases of pituitary apoplexy (a clinical syndrome secondary to infarction of the pituitary gland) have been reported after the administration of gonadotropin-releasing hormone agonists. In a majority of these cases, a pituitary adenoma was diagnosed, with a majority of pituitary apoplexy cases occurring within 2 weeks of the first dose, and some within the first hour. In these cases, pituitary apoplexy has presented as sudden headache, vomiting, visual changes, ophthalmoplegia, altered mental status, and sometimes cardiovascular collapse. Immediate medical attention has been required.

Cardiovascular adverse events: Cases of serious venous and arterial thromboembolism have been reported, including deep vein thrombosis, pulmonary embolism, myocardial infarction, stroke, and transient ischemic attack. Although a temporal relationship was reported in some cases, most cases were confounded by risk factors or concomitant medication use. It is unknown if there is a causal association between the use of GnRH analogs and these events.

Central/peripheral nervous adverse events: Convulsion.

Psychiatric adverse events: Mood swings, including depression; suicidal ideation and attempt.

Hepatic adverse events: Rarely reported serious liver injury.

Reproductive system adverse events: Cases of ovarian hyperstimulation syndrome have been reported with SYNAREL monotherapy when used for Assisted Reproductive Technology which is not an approved indication.

OVERDOSAGE

In experimental animals, a single subcutaneous administration of up to 60 times the recommended human dose (on a µg/kg basis, not adjusted for bioavailability) had no adverse effects. At present, there is no clinical evidence of adverse effects following overdosage of GnRH analogs.

Based on studies in monkeys, SYNAREL is not absorbed after oral administration.

DOSAGE AND ADMINISTRATION

For the management of endometriosis, the recommended daily dose of SYNAREL is 400 µg. This is achieved by one spray (200 µg) into one nostril in the morning and one spray into the other nostril in the evening. Treatment should be started between days 2 and 4 of the menstrual cycle.

In an occasional patient, the 400 µg daily dose may not produce amenorrhea. For these patients with persistent regular menstruation after 2 months of treatment, the dose of SYNAREL may be increased to 800 µg daily. The 800 µg dose is administered as one spray into each nostril in the morning (a total of two sprays) and again in the evening.

The recommended duration of administration is six months. Retreatment cannot be recommended since safety data for retreatment are not available. If the symptoms of endometriosis recur after a course of therapy, and further treatment with SYNAREL is contemplated, it is recommended that bone density be assessed before retreatment begins to ensure that values are within normal limits.

There appeared to be no significant effect of rhinitis, i.e., nasal congestion, on the systemic bioavailability of SYNAREL; however, if the use of a nasal decongestant for rhinitis is necessary during treatment with SYNAREL, the decongestant should not be used until at least 2 hours following dosing with SYNAREL.

Sneezing during or immediately after dosing with SYNAREL should be avoided, if possible, since this may impair drug absorption.

At 400 µg/day, a bottle of SYNAREL provides a 30-day (about 60 sprays) supply. If the daily dose is increased, increase the supply to the patient to ensure uninterrupted treatment for the recommended duration of therapy.

HOW SUPPLIED

Each 0.5 ounce bottle (NDC 0025-0166-08) contains 8 mL SYNAREL (nafarelin acetate) Nasal Solution 2 mg/mL (as nafarelin base), and is supplied with a metered spray pump that delivers 200 µg of nafarelin per spray. A dust cover and a leaflet of patient instructions are also included.

STORAGE AND HANDLING

Store upright at 25°C (77°F); excursions permitted to 15–30°C (59–86°F) [see USP Controlled Room Temperature]. Protect from light.

LAB-0173-14.0
Revised: November 2025

PATIENT INFORMATION

SYNAREL
nafarelin acetate
Nasal Spray

Patient Instructions for Use

Introduction

Your doctor has prescribed SYNAREL Nasal Solution to treat your symptoms of endometriosis. This pamphlet has two purposes:

1.) to review information your doctor has given you about SYNAREL; and
2.) to give you information about how to use SYNAREL properly.

Please read this pamphlet carefully. If you still have questions after reading it or if you have questions at any time during your treatment with SYNAREL, be sure to check with your doctor.

SYNAREL is used to relieve the symptoms of endometriosis. The lining of the uterus is called the endometrium, and part of it is shed during menses. In endometriosis, endometrial tissue is also found outside the uterus and, like normal endometrial tissue, can bleed during a menstrual cycle. It is, in part, this monthly activity that causes you to have symptoms during your cycle. Most often, this out-of-place endometrial tissue is found around the uterus, ovaries, the intestine or other organs in the pelvis. Although some women with endometriosis have no symptoms, many have problems such as severe menstrual cramps, pain during sexual intercourse, low back pain, and painful bowel movements.

Endometrial tissue is affected by the body's hormones, especially estrogen, which is made by the ovaries. When estrogen levels are low, endometrial tissue shrinks (perhaps even disappears), and symptoms of endometriosis ease. SYNAREL temporarily reduces estrogen in the body and temporarily relieves the symptoms of endometriosis.

Important Information about SYNAREL

1. You should not use SYNAREL if
  1. you are pregnant.
  2. you are breast feeding.
  3. you have abnormal vaginal bleeding that has not been checked into by your doctor.
  4. you are allergic to any of the ingredients of SYNAREL (nafarelin acetate, benzalkonium chloride, acetic acid, sodium hydroxide, hydrochloric acid, sorbitol, purified water).
2. SYNAREL is a prescription medicine that should be used according to your doctor's directions. SYNAREL comes as a special nasal spray that gives a measured amount of medicine. To be effective, SYNAREL must be used every day, twice a day, for the whole treatment period.
3. It is important to use a non-hormonal method of contraception (such as diaphragm with contraceptive jelly, IUD, condoms) while taking SYNAREL. You should not use birth control pills while taking SYNAREL.
4. If you miss 1 or more doses of SYNAREL, vaginal bleeding (often called breakthrough bleeding) may occur. If you miss successive doses of SYNAREL and have not been using contraception as described above, release of an egg from the ovary (ovulation) may occur, with the possibility of pregnancy. Under these circumstances you must see your physician to make sure you are not pregnant. If you should become pregnant while using SYNAREL, you must discuss the possible risks to the fetus and the choices available to you with your physician.
5. Because SYNAREL works by temporarily reducing the body's production of estrogen, a female hormone produced by the ovary, you may have some of the same changes that normally occur at the time of menopause, when the body's production of estrogen naturally decreases. For the first two months after you start using SYNAREL, you may experience some irregular vaginal spotting or bleeding. The duration and intensity of this bleeding may vary; it may be similar to your usual menstruation, or it may be lighter or heavier. The duration may also vary from brief to prolonged. In any case, you can expect this bleeding to stop by itself. After the first two months of treatment with SYNAREL, you can expect a decrease in menstrual flow, and your periods may stop altogether. However, if you miss one or more doses of SYNAREL, you may continue to experience vaginal bleeding. If you continue to experience normal menstrual cycles after two months use of SYNAREL, you should see your doctor about the continued periods. Other changes due to decreased estrogen include hot flashes, vaginal dryness, headaches, mood changes, and decreased interest in sex. Most of these changes are caused by low estrogen levels and may occur during treatment with SYNAREL. Some patients may also experience acne, muscle pain, reduced breast size, and irritation of the tissues inside the nose. These symptoms should disappear after you stop taking the drug.
6. When you take SYNAREL, your estrogen levels will be low. Low estrogen levels can result in a small loss of mineral from bone, some of which may not be reversible. During one six-month treatment period, this small loss of mineral from bone should not be important.
  There are certain conditions that may increase the possibility of the thinning of your bones when you take a drug such as SYNAREL. They are:
  1. excessive use of alcohol;
  2. smoking;
  3. family history of osteoporosis (thinning of the bones with fractures);
  4. taking other medications that can cause thinning of the bones.
    You should discuss the possibility of osteoporosis or thinning of the bones with your physician before starting SYNAREL. You should also be aware that repeat treatments are not recommended since they may put you at greater risk of bone thinning, particularly if you have the above conditions.
7. Depression may occur or worsen during treatment with GnRH agonists, including SYNAREL 2 mg/mL, especially in patients with a history of depression. Immediately report thoughts and behaviors of concern to your healthcare providers.
8. Severe cutaneous (skin) adverse reactions (SCARs) may happen with treatment with GnRH agonists like SYNAREL. Stop using SYNAREL and call your child’s doctor right away if your child has any of the following signs or symptoms during treatment with SYNAREL:

- skin rash or acne
- dry skin
- itching
- blisters on your skin
- redness or swelling of your face, hands, or soles of your feet

- blister or sores in your mouth
- peeling of your skin
- fever
- muscle or joint aches
- swollen glands

9. During studies, menstruation usually resumed within 2 to 3 months of stopping treatment with SYNAREL. At the end of treatment 60% of patients treated with SYNAREL were symptom free, 32% had mild symptoms, 7% had moderate symptoms and 1% had severe symptoms.
  Of the 60% of patients who had complete relief of symptoms at the end of treatment, 17% had moderate symptoms at the end of the six month post-treatment period; 33% had mild symptoms; 50% were symptom free; no patient had severe symptoms.
10. Retreatment cannot be recommended since the safety of such retreatment is not known.
11. It is all right to use a nasal decongestant spray while you are being treated with SYNAREL if you follow these simple rules. Use SYNAREL first. Wait at least 2 hours after using SYNAREL before you use the decongestant spray.
12. You should avoid sneezing during or immediately after using SYNAREL, if possible, since sneezing may impair drug absorption.

Proper use of SYNAREL for Treatment of Endometriosis

1. When you start to use SYNAREL, the first dose should be taken between the second and fourth day after the beginning of your menstrual bleeding. You should continue taking SYNAREL every day as prescribed.
  Do not miss a single dose.
2. Unless your doctor has given you special instructions, follow the steps for using SYNAREL twice each day, about 12 hours between doses:
  1. once in the morning in one nostril (for example, 7 a.m.)
  2. once in the evening in the other nostril (for example, 7 p.m.)
    The length of treatment is usually about 6 months, unless your doctor has given you special instructions.
3. Because it is so important that you do not miss a single dose of SYNAREL, here are some suggestions to help you remember:
  1. Keep your SYNAREL in a place where you will be reminded to use it each morning and each evening — next to your toothbrush is one possibility.
  2. Keep track of each dose on a calendar.
  3. Make a note on your calendar on the day you start a new bottle of SYNAREL. You can also mark the date you started right on the bottle. Be sure to refill your prescription before the 30 days are up so you will have a new bottle on hand.
4. A bottle of SYNAREL should not be used for longer than 30 days (60 sprays). Each bottle contains sufficient quantity of nasal solution for initial priming of the pump and 30 days (60 sprays) of treatment. At the end of 30 days, a small amount of liquid will be left in the bottle. Do not try to use up that leftover amount because you might get too low a dose, which could interfere with the effectiveness of your treatment. Dispose of the bottle and do not reuse.
5. If your doctor increases your daily dose of SYNAREL, then your bottle will not last the standard 30 days. Please discuss this with your doctor to be sure that you have an adequate supply for uninterrupted treatment with SYNAREL to complete the recommended treatment period.

Preparation of the SYNAREL Nasal Spray unit

For use in your nose only.

Before you use SYNAREL nasal spray for the first time, you will need to prime it. This will ensure that you get the right dose of medicine each time you use it.

Important Tips about using SYNAREL

- Your pump should produce a fine mist, which can only happen by a quick and firm pumping action. It is normal to see some larger droplets of liquid within the fine mist. However, if SYNAREL comes out of the pump as a thin stream of liquid instead of a fine mist, SYNAREL may not work as well, and you should talk to your pharmacist.
- Be sure to clean the Spray Tip before and after every use. (See Step 4). Failure to do this may result in a clogged tip that may cause you not to get the right amount of medicine that is prescribed for you.
- The pump is made to deliver only a set amount of medicine, no matter how hard you pump it.
- Do Not try to make the tiny hole in the spray tip larger. If the hole is made larger the pump will deliver a wrong dose of SYNAREL.

Figure A

To Prime the Pump:

Figure B

1. Remove and save the white safety clip and the clear plastic dust cover from the spray bottle (See Figure B).

Figure C

2. Hold the bottle in an upright position away from you. Put two fingers on the "shoulders" of the spray bottle and put your thumb on the bottom of the bottle. Apply pressure evenly to the "shoulders" and push down quickly and firmly 7 to 10 times, until you see a fine spray. Usually you will see the spray after about 7 pumps. (See Figure C).

3. The pump is now primed. Priming only needs to be done 1 time, when you start using a new bottle of SYNAREL. You will waste your medicine if you prime the pump every time you use it and may not have enough medicine for 30 days of treatment.

Figure D

4. Clean the Spray Tip after Priming:
  1. Hold the bottle in a horizontal position. Rinse the spray tip with warm water while wiping the tip with your finger or soft cloth for 15 seconds.
  2. Wipe the spray tip with a soft cloth or tissue to dry.
  3. Replace the white safety clip and the clear plastic dust cover on the spray bottle (See Figure D).
  4. Do Not try to clean the spray tip using a pointed object. Do Not take apart the pump.

How to use the SYNAREL Nasal Spray unit for the treatment of Endometriosis

Figure E

5. Gently blow your nose to clear both nostrils before you use SYNAREL nasal spray (See Figure E).

Figure F

6. Clean the Spray Tip. Remove and save the white safety clip and the clear plastic dust cover from the spray bottle (See Figure F).
  1. Hold the bottle in a horizontal position. Rinse the spray tip with warm water while wiping the tip with your finger or soft cloth for 15 seconds.
  2. Wipe the spray tip with a soft cloth or tissue to dry.
  3. Do Not try to clean the spray tip using a pointed object.
  4. Do Not try to take apart the pump.

Figure G

7. Bend your head forward and put the spray tip into one nostril. The tip should not reach too far into your nose. Aim the spray tip toward the back and outer side of your nose (See Figure G).

Figure H

8. Close the other nostril with your finger (See Figure H).

9. Apply pressure evenly to the "shoulders" and push down quickly and firmly. Pump the sprayer 1 time, at the same time as you sniff in gently. If the sprayer fails to deliver the dose clean the spray tip (See Step 6 Clean the Spray Tip).

Figure I

10. Remove the spray tip from your nose and tilt your head backwards for a few seconds. This lets the SYNAREL spray spread over the back of your nose (See Figure I).
  Do not spray in your other nostril unless your doctor has instructed you to do so.

Figure J

11. Clean the Spray Tip after use (See Step 4).

It is important that you clean the spray tip before and after every use. Failure to do this may result in a clogged tip that may cause you to get the wrong dose of medicine.

Important Reminder: Treatment with SYNAREL must be uninterrupted with no missed doses to be effective.
Make sure you use SYNAREL exactly as your doctor tells you. Make sure to note the date you start each bottle so you do not run out of medicine and miss doses.

Keep out of the reach of children and use carefully as directed.

Storage Instructions:

- Store SYNAREL at 59°F to 86°F (15°C to 30°C).
- Store the SYNAREL bottle upright.
- Keep SYNAREL out of the light.
- Do not freeze SYNAREL.

This product's label may have been updated. For current full prescribing information, please visit www.pfizer.com.

LAB-0278-10.0
Revised: November 2025

MEDICATION GUIDE
SYNAREL (sin-na-rell)
(nafarelin acetate) nasal solution

What is the most important information I should know about SYNAREL?

- Some people taking GnRH agonists like SYNAREL have had new or worsened mental (psychiatric) problems. Mental (psychiatric) problems may include emotional symptoms such as:
  - crying
  - irritability
  - restlessness (impatience)
  - anger
  - acting aggressive

Call your child's doctor right away if your child has any new or worsening mental symptoms or problems while taking SYNAREL

- Some people taking GnRH agonists like SYNAREL have had seizures. The risk of seizures may be higher in people who:
  - have a history of seizures.
  - have a history of epilepsy.
  - have a history of brain or brain vessel (cerebrovascular) problems or tumors.
  - are taking a medicine that has been connected to seizures such as taking bupropion or selective serotonin reuptake inhibitors (SSRIs).

Seizures have also happened in people who have not had any of these problems.
Call your child's doctor right away if your child has a seizure while taking SYNAREL.
Severe cutaneous (skin) adverse reactions may happen during treatment with GnRH agonists like SYNAREL. Stop using SYNAREL and call your child’s doctor right away if your child has any of the following signs or symptoms during treatment with SYNAREL:

- skin rash or acne
- dry skin
- itching
- blisters on your skin
- redness or swelling of your face, hands, or soles of your feet

- blisters or sores in your mouth
- peeling of your skin
- fever
- muscle or joint aches
- swollen glands

What is SYNAREL?
SYNAREL is a gonadotropin releasing hormone (GnRH) medicine used for the treatment of children with central precocious puberty (CPP).

Do not give SYNAREL if your child:

- is allergic to gonadotropin releasing hormone (GnRH), GnRH agonist medicines, or any of the ingredients in SYNAREL. See the end of this Medication Guide for a complete list of ingredients in SYNAREL.
- has unusual vaginal bleeding that has not been checked by her doctor.
- is pregnant or may become pregnant. SYNAREL can cause birth defects or loss of the baby. If your child becomes pregnant call your doctor.
- is breastfeeding or plans to breastfeed. It is not known if SYNAREL passes into breast milk. You and your child's doctor should decide if your child will take SYNAREL or breastfeed. Do not breastfeed while taking SYNAREL.

Before your child takes SYNAREL, tell your doctor about all of your child's medical conditions, including if they:

- have a history of mental (psychiatric) problems.
- have or have had a history of seizures.
- have a history of epilepsy.
- have a history of brain or brain vessel (cerebrovascular) problems or tumors
- are taking a medicine that has been connected to seizures such as bupropion or selective serotonin reuptake inhibitors (SSRIs).

Tell your doctor about all the medicines your child takes, including prescription and over-the-counter medicines, vitamins, and herbal supplements.

How should your child take SYNAREL?

- Your child's doctor should do tests to make sure your child has CPP before treating your child with SYNAREL.
- Keep all scheduled visits to the doctor. If scheduled doses are missed, your child may start having signs of puberty again. The doctor will do regular exams and blood tests to check for signs of puberty.
- Take SYNAREL exactly as your doctor tells you to take it. See detailed "Instructions for Use" at the end of this Medication Guide for information about the right way to use SYNAREL.
- Your child's doctor will tell you how much SYNAREL your child is to take and when to take it. If your doctor increases your child's daily dose of SYNAREL, 1 bottle will not last the standard 7 days. Talk with your child's doctor to make sure your child has enough SYNAREL to take their prescribed dose every day.

What should your child avoid while taking SYNAREL?

- Your child should avoid sneezing while taking SYNAREL or right after using it, if possible. This could reduce the amount of medicine your child's body absorbs.
- If your child needs to use a nasal decongestant spray while being treated with SYNAREL, they should not use the decongestant spray for at least 2 hours after taking the dose of SYNAREL.

What are the possible side effects of SYNAREL?
SYNAREL may cause serious side effects, including:

- See "What is the most important information I should know about SYNAREL"
- in the first month of treatment, SYNAREL can cause an increase in some hormones. During this time you may notice more signs of puberty in your child, including vaginal bleeding and breast enlargement in girls. Within 1 month of treatment, you should see signs in your child that puberty is stopping.
- increased pressure in the fluid around the brain can happen in children taking gonadotropin releasing hormone (GnRH) agonist medicines including SYNAREL. Call your child's doctor right away if your child has any of the following symptoms during treatment with SYNAREL:

- headache
- eye problems, including blurred vision
- double vision and decreased eyesight
- eye pain

- ringing in the ears
- dizziness
- nausea

The side effects of SYNAREL include:

- allergic reactions such as shortness of breath, chest pain, hives, rash, and itching
- acne
- temporary increase in pubic hair
- body odor
- flaky, scaly skin
- hot flashes
- stuffy or runny nose (rhinitis)
- white or brown vaginal discharge

These are not all of the possible side effects of SYNAREL. Call your doctor for medical advice about side effects. You may report side effects to FDA at 1-800-FDA-1088.

General Information about the safe and effective use of SYNAREL.
Medicines are sometimes prescribed for purposes other than those listed in a Medication Guide. Do not use SYNAREL for a condition for which it is not prescribed. Do not give SYNAREL to other people, even if they have the same symptoms that you have. It may harm them.
You can ask your doctor or pharmacist for information about SYNAREL that is written for health professionals.

What are the ingredients in SYNAREL?
Active ingredient: nafarelin acetate
Inactive ingredients: benzalkonium chloride, glacial acetic acid, sodium hydroxide or hydrochloric acid (to adjust pH), sorbitol, and purified water

PATIENT INFORMATION

Instructions for Use
SYNAREL (sin-na-rell)
(nafarelin acetate)
nasal solution

For use in the nose only.

Figure A

Before you use SYNAREL nasal spray for the first time, you will need to prime it. This will make sure that you get the right dose of medicine each time you use it. Priming only needs to be done 1 time, when you start using a new bottle of SYNAREL.

To Prime the Pump:

Figure B

1. Remove and save the white safety clip and the clear plastic dust cover from the spray bottle (See Figure B).

Figure C

2. Hold the bottle in an upright position away from you. Put 2 fingers on the "shoulders" of the spray bottle and put your thumb on the bottom of the bottle. Apply pressure evenly to the "shoulders" and push down quickly and firmly 7 to 10 times, until you see a fine mist spray. Usually you will see the spray after about 7 pumps. (See Figure C). The pump is now primed.
  It is normal to see some larger droplets of liquid within the fine mist. However, if SYNAREL comes out of the pump as a thin stream of liquid instead of a fine mist, SYNAREL may not work as well, and you should talk to your pharmacist.

Figure D
Figure E

3. Clean the Spray Tip after Priming:
  1. Hold the bottle in sideways (horizontal) position (see Figure D).
    Rinse the "spray tip" with warm water while wiping the tip with your finger or soft cloth for 15 seconds.
  2. Wipe the spray tip with a soft cloth or tissue to dry.
  3. Replace the white safety clip and the clear plastic dust cover on the spray bottle. (See Figure E).
  4. Do not try to clean the spray tip using a pointed object.
  5. Do not take apart the pump.

How to use the SYNAREL Nasal Spray for the treatment of Central Precocious Puberty

Figure F

4. Have your child blow their nose to clear both nostrils before using SYNAREL nasal spray (see Figure F). If the child is too young to blow their nose, you may need to clear the child's nostrils with a bulb syringe.

Figure G

5. Clean the Spray Tip each time before and after using SYNAREL.
  1. Remove and save the white safety clip and the clear plastic dust cover from the spray bottle (See Figure G).
  2. Hold the bottle in sideways (horizontal) position. Rinse the spray tip with warm water while wiping the tip with your finger or soft cloth for 15 seconds.
  3. Wipe the spray tip with a soft cloth or tissue to dry.
  4. Do not try to clean the spray tip using a pointed object.
  5. Do not try to take apart the pump.

Figure H

6. The child's head should be bent back a little and the spray tip put into one nostril. The tip should not reach too far into the nose. Aim the spray tip toward the back and outer side of the nose (See Figure H).

Figure I

7. Close the other nostril with a finger (See Figure I).

Put pressure evenly to the "shoulders" and push down quickly and firmly. Pump the sprayer 1 time, at the same time as the child sniffs in gently. Wait about 30 seconds and put one more spray in the same nostril. Repeat this process in the other nostril, for a total of four sprays. If the sprayer fails to deliver the dose, clean the spray tip (See Step 5 Clean the Spray Tip each time before and after using SYNAREL).

Figure J

8. Remove the spray tip from the child's nose after all sprays are completed. Keep the child's head tilted back for a few seconds. This lets the SYNAREL spray spread over the back of the nose (See Figure J).

Figure K

9. Clean the Spray Tip after use (See Step 5. Put on the white safety clip and the clear plastic dust cover (see Figure K).

It is important that you clean the spray tip before and after every use. Not doing this may result in a clogged tip that may cause you to get the wrong dose of medicine.

How should I store SYNAREL?

- Store SYNAREL at room temperature between 59°F to 86°F (15°C to 30°C).
- Store the SYNAREL bottle upright.
- Keep SYNAREL out of the light.

Keep SYNAREL and all medicines out of the reach of children.

For more information call 1-800-438-1985.

This Medication Guide and Instructions for Use have been approved by the U.S. Food and Drug Administration.

Manufactured for: Pfizer Inc., 235 East 42nd Street, New York, NY, 10017

LAB-1049-4.0
Revised: November 2025

PRINCIPAL DISPLAY PANEL - 8 mL Bottle Label

ALWAYS DISPENSE WITH MEDICATION GUIDE

Pfizer
NDC 0025-0166-08

Synarel®
(nafarelin acetate) nasal solution

2 mg/mL (as nafarelin base)

SPRAY - FOR INTRANASAL USE ONLY.
Each actuation delivers approximately
200 mcg nafarelin.

8 mL (60 metered sprays)
Rx only

PRINCIPAL DISPLAY PANEL - 8 mL Bottle Carton

ALWAYS DISPENSE WITH MEDICATION GUIDE

Pfizer
NDC 0025-0166-08

Synarel®
(nafarelin acetate) nasal solution

2 mg/mL (as nafarelin base)

SPRAY – FOR INTRANASAL USE ONLY

Each actuation delivers approximately
200 mcg nafarelin.

Carton contains: 1 bottle of nasal solution with
spray pump, patient information and complete
prescribing information.

Store upright.

8 mL (60 metered sprays)
Rx only